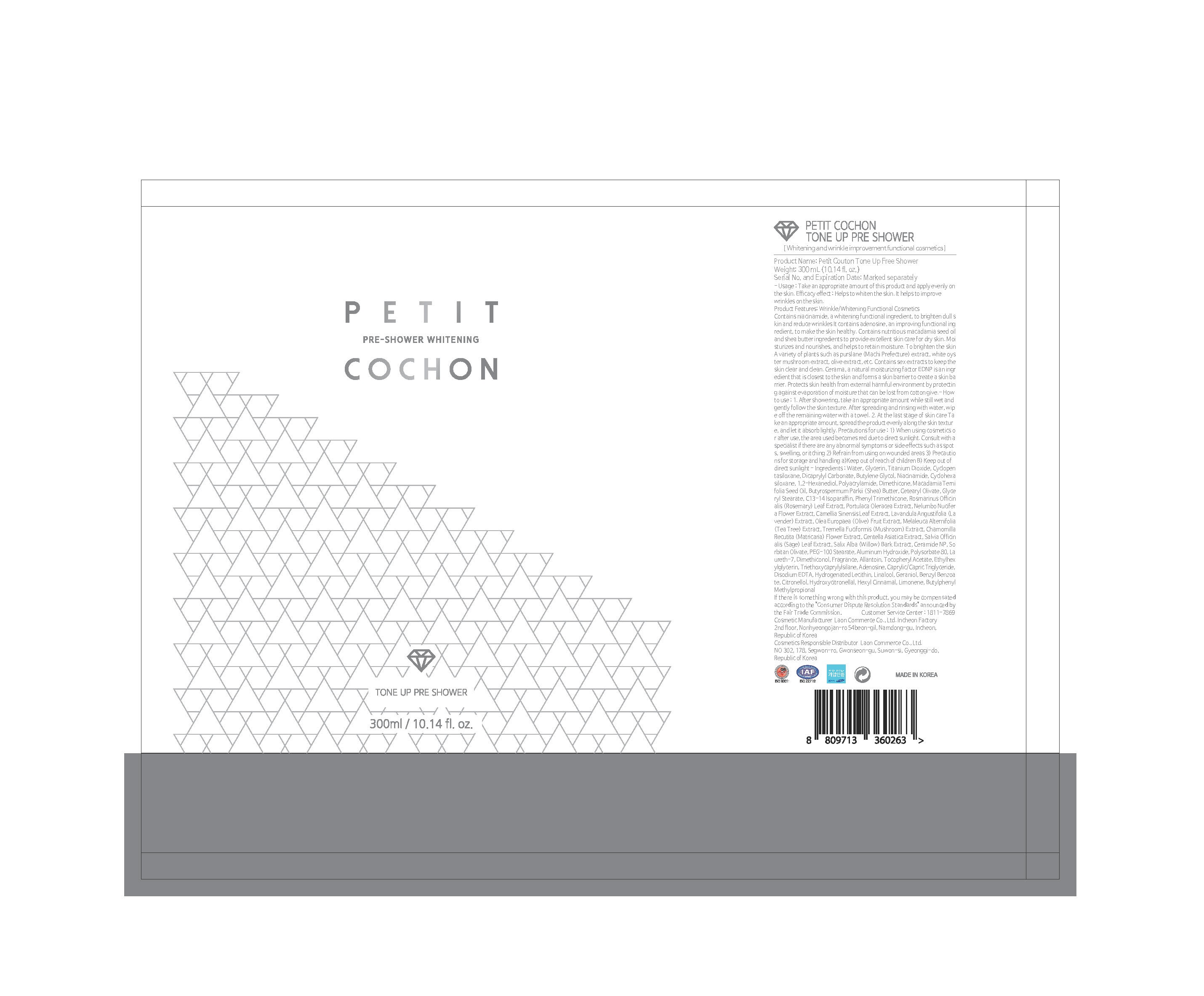 DRUG LABEL: PETIT COCHON TONE UP PRE SHOWER
NDC: 82083-0005 | Form: LIQUID
Manufacturer: LAON COMMERCE co ltd
Category: otc | Type: HUMAN OTC DRUG LABEL
Date: 20211024

ACTIVE INGREDIENTS: NIACINAMIDE 2 g/100 mL; ADENOSINE 0.04 g/100 mL
INACTIVE INGREDIENTS: WATER

ACTIVE INGREDIENT

niacinamide, adenosine

INACTIVE INGREDIENT

Water
Glycerin
Titanium Dioxide
Cyclopentasiloxane
Dicaprylyl Carbonate
Butylene Glycol
Cyclohexasiloxane
1,2-Hexanediol
Polyacrylamide
Dimethicone
Macadamia Ternifolia Seed Oil
Butyrospermum Parkii (Shea) Butter
Cetearyl Olivate
Glyceryl Stearate
C13-14 Isoparaffin
Phenyl Trimethicone
Rosmarinus Officinalis (Rosemary) Leaf Extract
Portulaca Oleracea Extract
Nelumbo Nucifera Flower Extract
Camellia Sinensis Leaf Extract
Lavandula Angustifolia (Lavender) Extract
Olea Europaea (Olive) Fruit Extract
Melaleuca Alternifolia (Tea Tree) Extract
Tremella Fuciformis (Mushroom) Extract
Chamomilla Recutita (Matricaria) Flower Extract
Centella Asiatica Extract
Salvia Officinalis (Sage) Leaf Extract
Salix Alba (Willow) Bark Extract
Ceramide NP
Sorbitan Olivate
PEG-100 Stearate
Aluminum Hydroxide
Polysorbate 80
Laureth-7
Dimethiconol
Fragrance
Allantoin
Tocopheryl Acetate
Ethylhexylglycerin
Triethoxycaprylylsilane
Caprylic/Capric Triglyceride
Disodium EDTA
Hydrogenated Lecithin
Linalool
Geraniol
Benzyl Benzoate
Citronellol
Hydroxycitronellal
Hexyl Cinnamal
Limonene
Butylphenyl Methylpropional

PURPOSE

whitening wrinkle improvement

WARNINGS

■ if following abnormal symptoms persist, discontinue use

Irritation around the eyes, ears, mucous membranes, including the mouth, under the skin irritation and rashes

■ Stop immediately and consult a doctor if you experience

1) Hypersensitivity symptoms such as erythema, itching and dermatitis.

2) Skin Irritation

3) Following Instructions when using medication

(1) For external use only (Do not use internally)

(2) Avoid getting into the eyes (if contact occurs, wash well with clean water)

Keep Out of Reach of Children.

INDICATIONS AND USAGE

After facial wash, use a toner, Put the ma

sk sheet on your face and take it off after 10~20 minutes.

DOSAGE AND ADMINISTRATION

for external use only